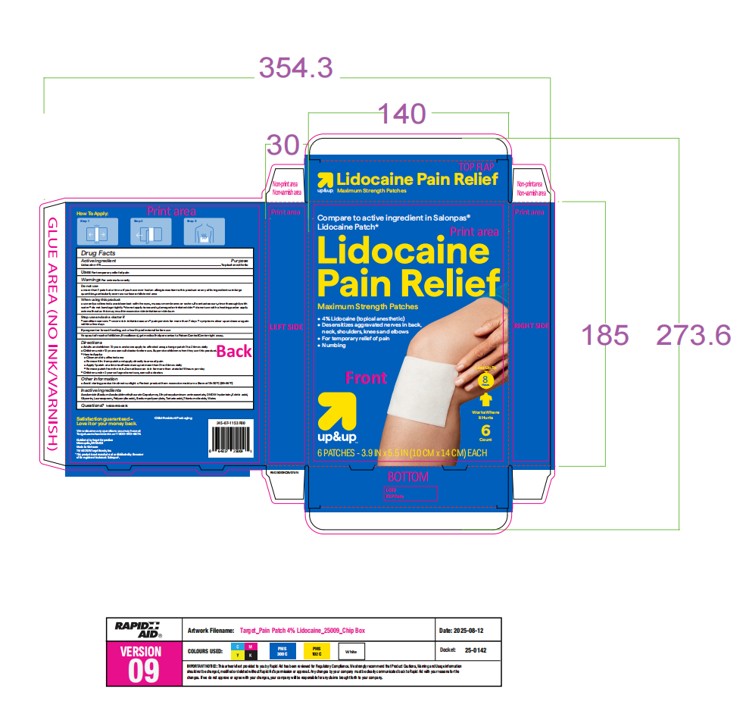 DRUG LABEL: Up up
NDC: 82442-744 | Form: PATCH
Manufacturer: Target Corporation
Category: otc | Type: HUMAN OTC DRUG LABEL
Date: 20251120

ACTIVE INGREDIENTS: LIDOCAINE 4 g/100 g
INACTIVE INGREDIENTS: WATER; DMDM HYDANTOIN; ACRYLAMIDE/SODIUM ACRYLOYLDIMETHYLTAURATE COPOLYMER (120000 MPA.S AT 1%); TITANIUM DIOXIDE; POLYACRYLIC ACID (800000 MW); GLYCERIN; EDETIC ACID; SODIUM POLYACRYLATE (8000 MW); TARTARIC ACID; LAUROCAPRAM; DIHYDROXYALUMINUM AMINOACETATE

Active Ingredient(s)

Lidocaine 4 % w/w

Purpose

Topical anesthetic

Use

For temporary relief of pain.

Warnings

For external use only.

Do not use

More than 1 patch at a time
If you are allergic to any ingredients of this product

In large quantities, particularly over raw surface or blistered areas.

When using this product:

Use only as directed

Do not bandage tightly

Avoid contact with eyes, mucous membranes or rashes

If contact occurs, rinse thoroughly with water.

Do not apply to wounds, damaged or irritation skin.

Do not use with a heating pad such as electric heating pad, as this may result in excessive skin irritation or skin burn.

Stop use and ask a doctor if:

Condition worsens

Severe skin irritation occurs

Symptoms persist for more than 7 days

Symptoms clear up and occur again within a few days

If pregnant or breastfeeding, ask a health professional before use.

Keep out of reach of children. If swallowed, get medical help or contact a Poison Control Center right away.

Directions

Adults and children 12 years of age and older: apply to affected area; changes patch 1 to 2 daily.

Children under 12 years of age: consult a doctor. Supervise children when they use this product

How to apply:

Clean and dry affected area

Remove film from patch and apply directly to area of pain

Apply 1 patch at a time to the affected area, not more than 3 to 4 times daily.

Remove patch from the skin. Do not leave on skin for more than a total of 8 hours per day.

Children under 12 years of age: do not use, consult a doctor.

Other information

Store between 15-30℃(59-86℉)

Protect product from excessive moisture

Avoid storing product in direct sunlight

Inactive ingredients

Acyclmide/Sodium Acryloyldimethyltaurate copolyme, Dihydroxyaluminum aminoacetetel, DMDM hydantoin, Edetic acid, Glycerin, Polyacrylic acid, Sodium polyacrylate, Tartaric acid, Titanium dioxide, Water